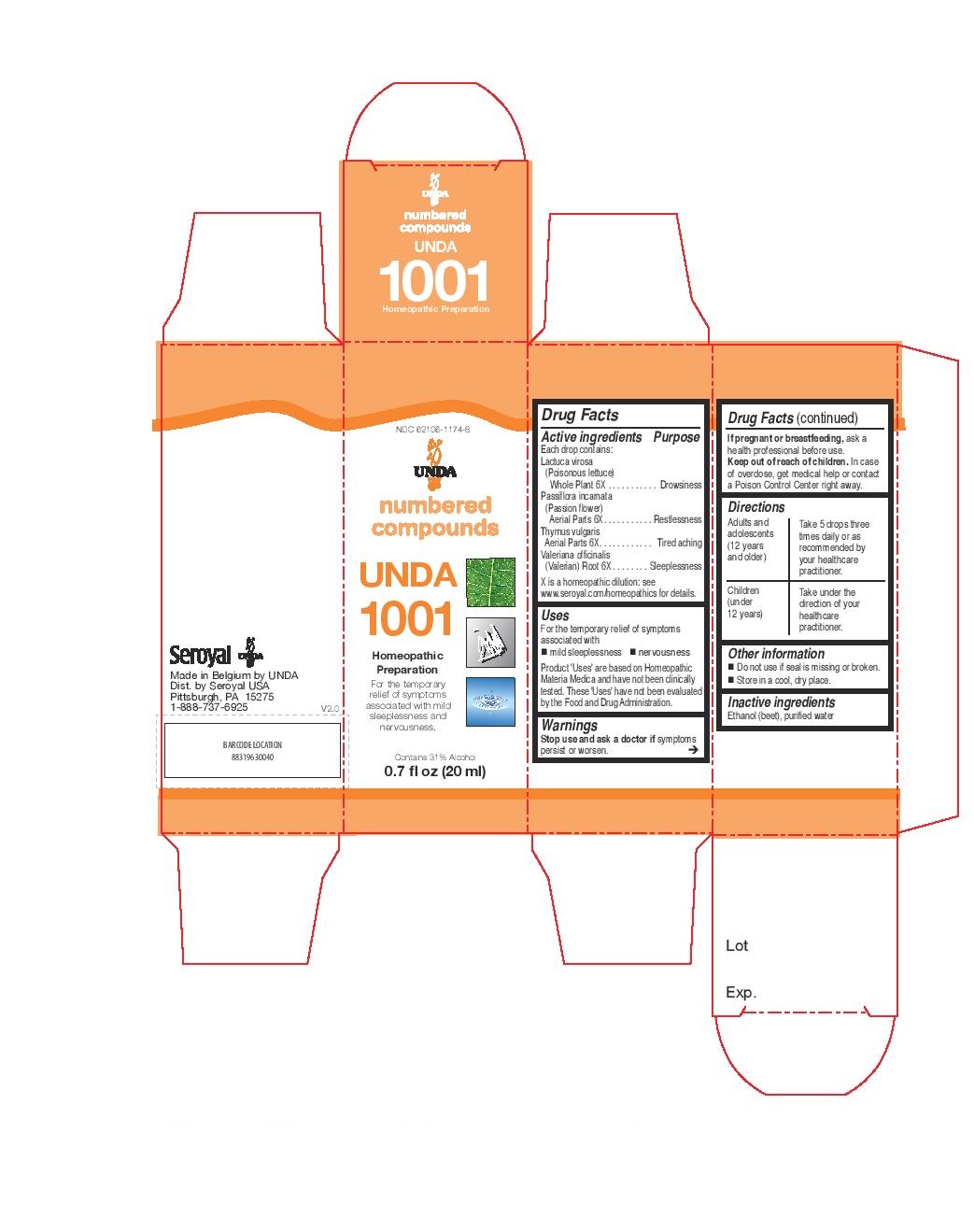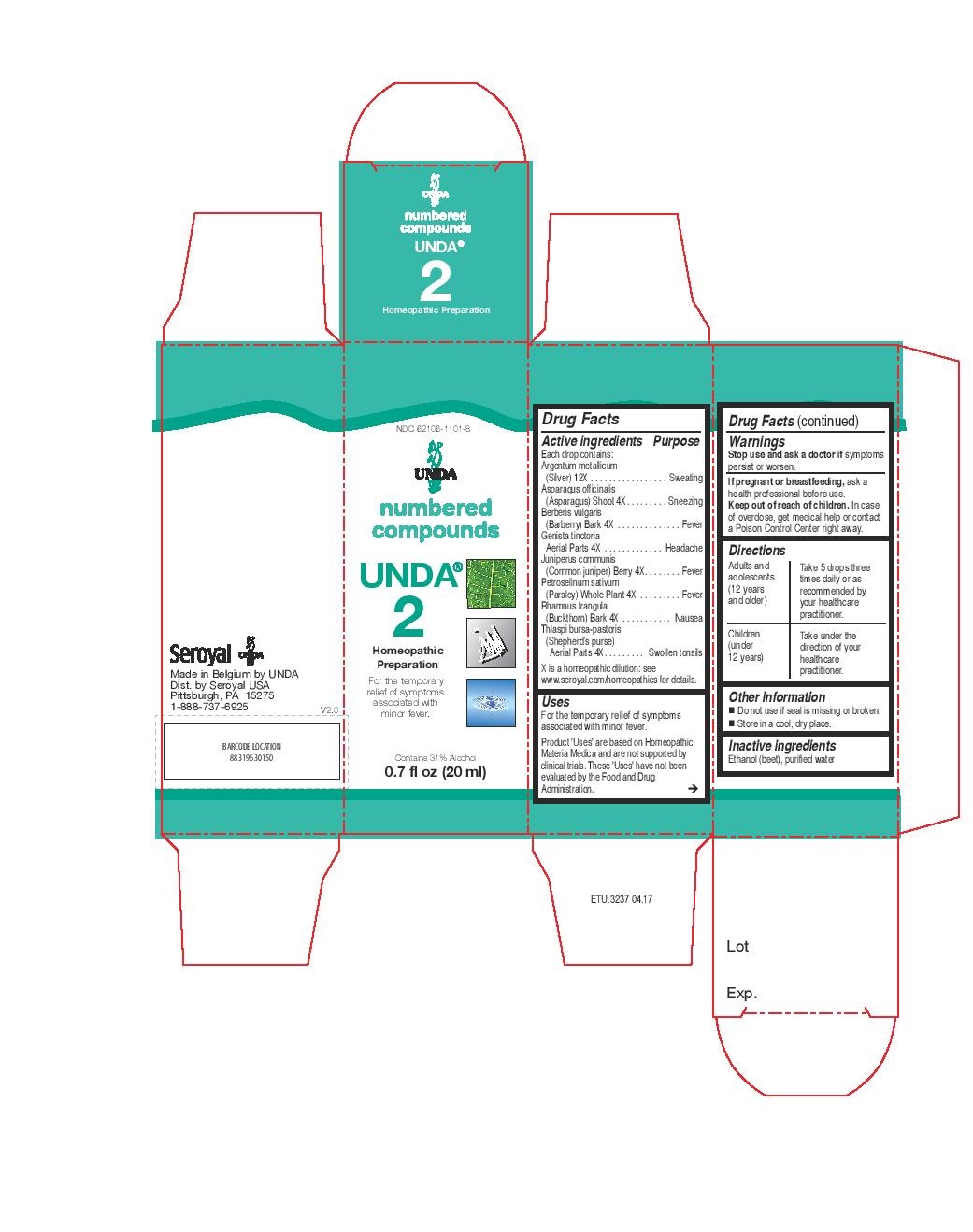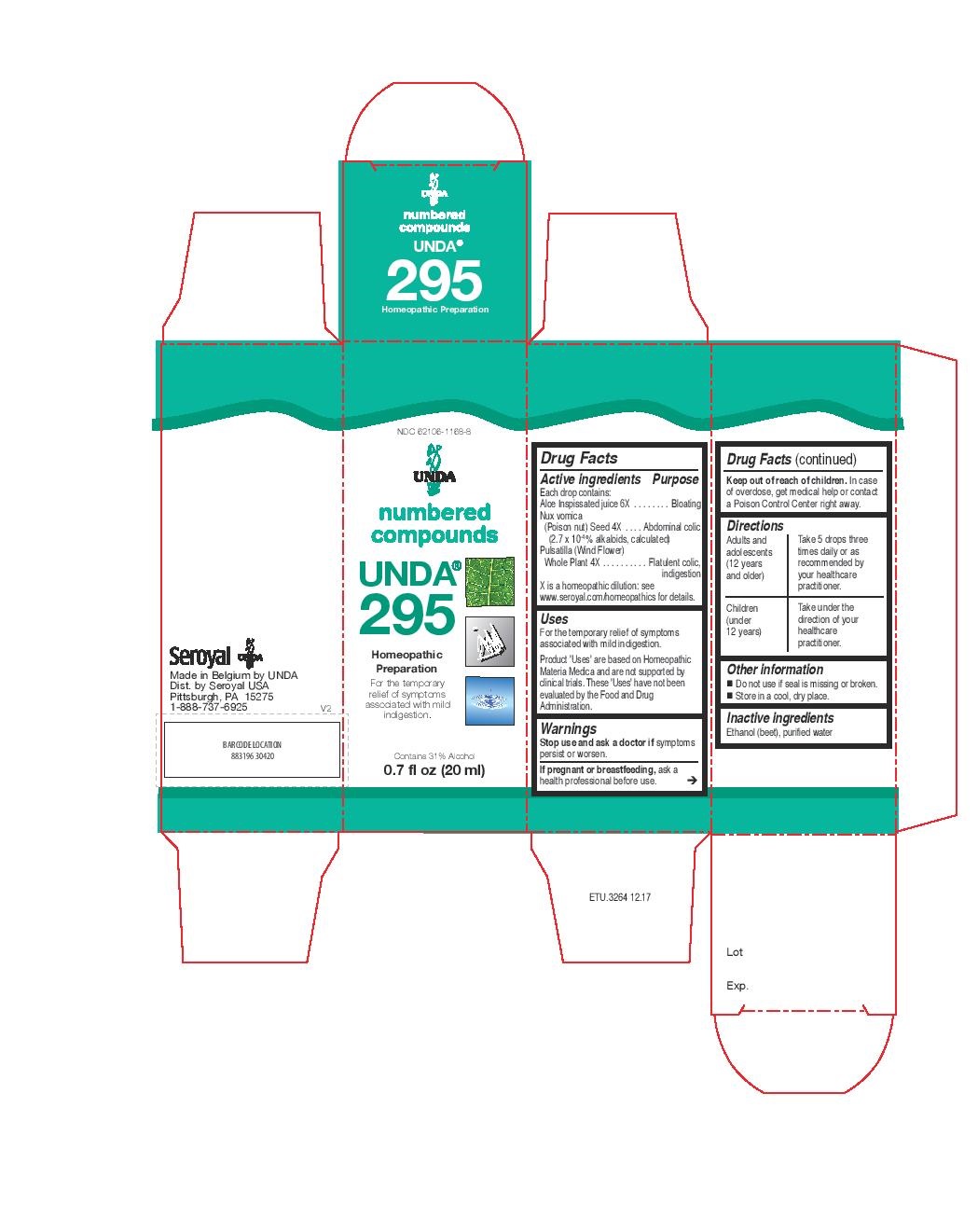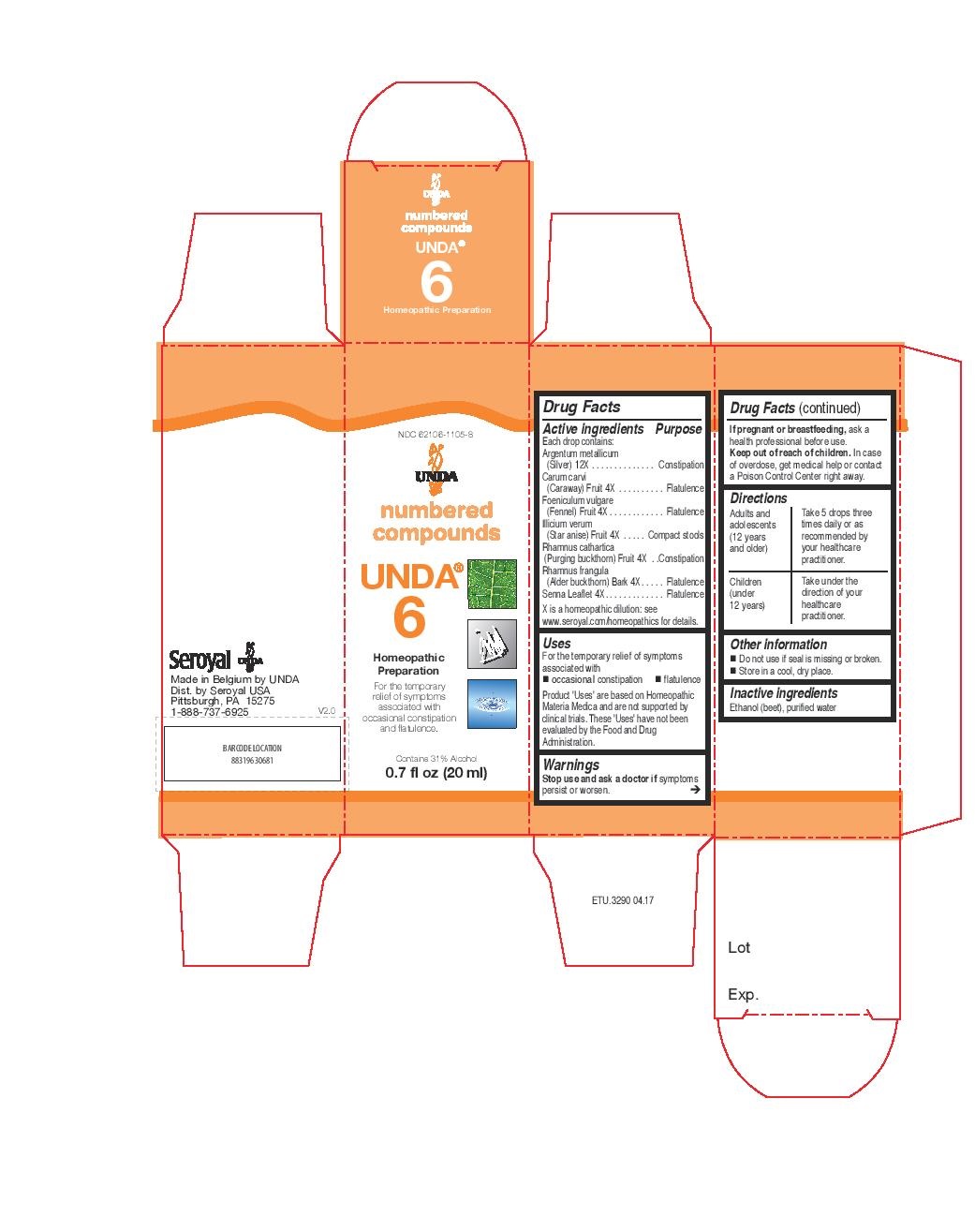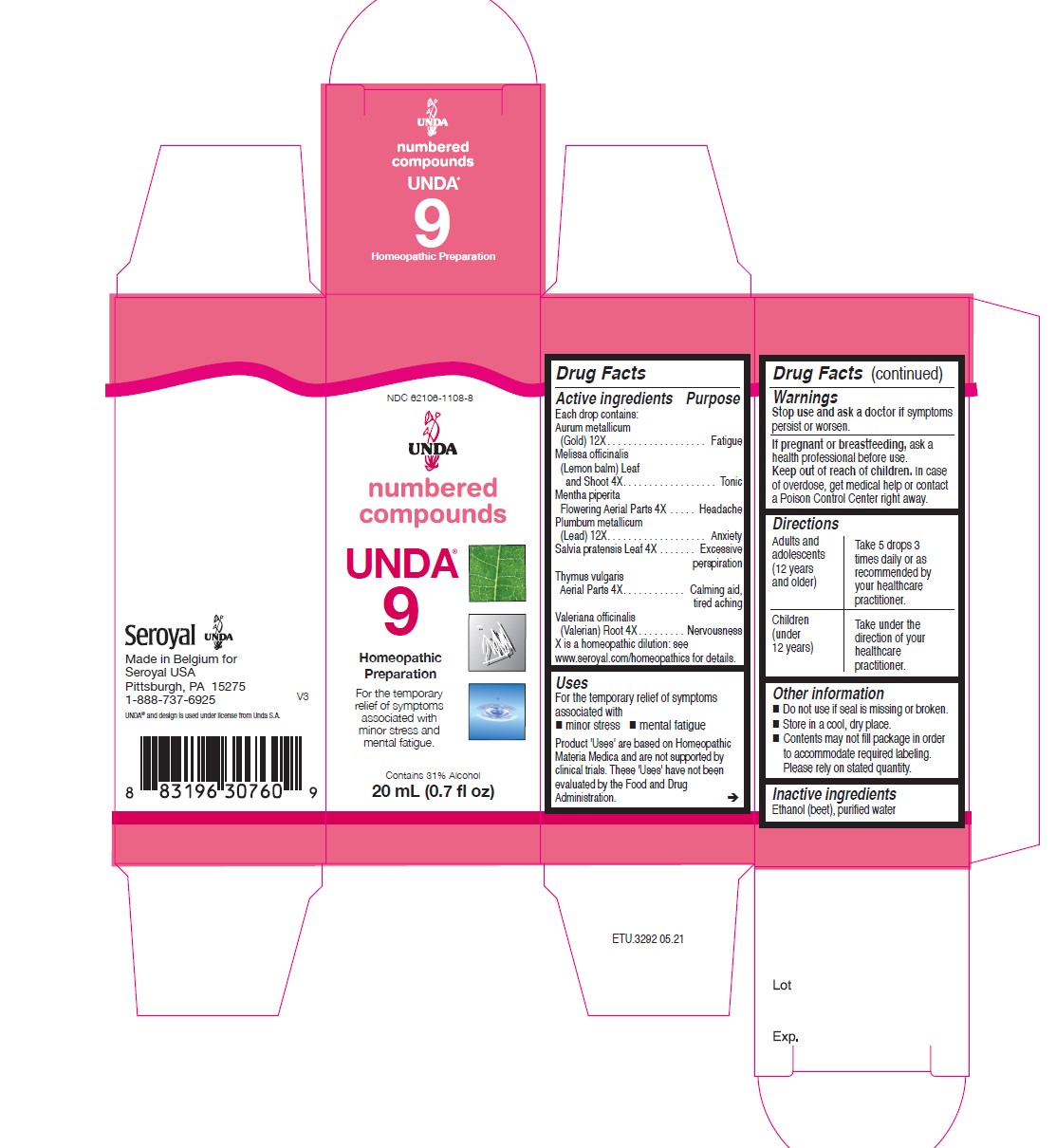 DRUG LABEL: UNDA 6
NDC: 62106-1105 | Form: LIQUID
Manufacturer: Seroyal USA
Category: homeopathic | Type: HUMAN OTC DRUG LABEL
Date: 20221025

ACTIVE INGREDIENTS: SENNA LEAF 4 [hp_X]/20 mL; FRANGULA ALNUS BARK 4 [hp_X]/20 mL; CARAWAY SEED 4 [hp_X]/20 mL; FENNEL SEED 4 [hp_X]/20 mL; ILLICIUM VERUM WHOLE 4 [hp_X]/20 mL; RHAMNUS CATHARTICA FRUIT 4 [hp_X]/20 mL; SILVER 12 [hp_X]/20 mL
INACTIVE INGREDIENTS: ALCOHOL; WATER

Unda Numbers

Active ingredients
Each drop contains:
Argentum metallicum (Silver) 12X
Asparagus officinalis (Asparagus) Shoot 4X
Berberis vulgaris (Barberry) Bark 4X
Genista tinctoria Aerial Parts 4X
Juniperus communis (Common juniper) Berry 4X
Petroselinum sativum (Parsley) Whole Plant 4X
Rhamnus frangula (Buckthorn) Bark 4X
Thlaspi bursa-pastoris (Shepherd’s purse) Aerial Parts 4X

Uses
For the temporary relief of symptoms associated with minor fever.

Warnings
Stop use and ask a doctor if symptoms persist or worsen.
If pregnant or breastfeeding, ask a health professional before use.
Keep out of reach of children. In case of overdose, get medical help or contact
a Poison Control Center right away.

PREGNANCY OR BREAST FEEDING

If pregnant or breastfeeding, ask a health professional before use.

Keep out of reach of children.

OVERDOSAGE

In case of overdose, get medical help or contact a Poison Control Center right away.

Stop use and ask a doctor if symptoms persist or worsen.

Inactive Ingredients:

Ethanol (beet),
purified water

Other information
Do not use if seal is missing or broken.
Store in a cool, dry place.

Directions
Adults and adolescents (12 years and older): Take 5 drops three times daily or as
recommended by your healthcare practitioner.
Children (under 12 years): Take under the direction of your
healthcare practitioner.

Uses
For the temporary relief of symptoms associated with minor fever.

Directions
Adults and adolescents (12 years and older): Take 5 drops three times daily or as
recommended by your healthcare practitioner.
Children (under 12 years): Take under the direction of your
healthcare practitioner.

Active ingredients

Each drop contains:
Argentum metallicum (Silver) 12X
Carum carvi (Caraway) Fruit 4X
Foeniculum vulgare (Fennel) Fruit 4X
Illicium verum (Star anise) Fruit 4X
Rhamnus cathartica (Purging buckthorn) Fruit 4X
Rhamnus frangula (Alder buckthorn) Bark 4X
Senna Leaflet 4X

Uses

For the temporary relief of symptoms associated with occasional constipation and flatulence.

Warnings
Stop use and ask a doctor if symptoms persist or worsen.

If pregnant or breastfeeding, ask a health professional before use.
Keep out of reach of children. In case of overdose, get medical help or contact
a Poison Control Center right away.

PREGNANCY OR BREAST FEEDING

If pregnant or breastfeeding, ask a healthcare professional before use.

Keep out of reach of children.

OVERDOSAGE

In case of overdose, get medical help or contact a Poison Control Center right away.

Stop use and ask a doctor if symptoms persist or worsen.

Inactive Ingredients:

Ethanol (beet),
purified water

Directions
Adults and adolescents (12 years and older): Take 5 drops three times daily or as
recommended by your healthcare practitioner.
Children (under 12 years): Take under the direction of your
healthcare practitioner.

Uses

For the temporary relief of symptoms associated with occasional constipation and flatulence.

Directions
Adults and adolescents (12 years and older): Take 5 drops three times daily or as
recommended by your healthcare practitioner.
Children (under 12 years): Take under the direction of your
healthcare practitioner.

Active ingredients
Each drop contains:
Aurum metallicum (Gold) 12X
Melissa officinalis (Lemon balm) Leaf and Shoot 4X
Mentha piperita Aerial Parts 4X
Plumbum metallicum (Lead) 12X
Salvia pratensis Leaf 4X
Thymus vulgaris Aerial Parts 4X
Valeriana officinalis (Valerian) Root 4X

Uses
For the temporary relief of symptoms associated with minor stress and mental fatigue.

Warnings
Stop use and ask a doctor if symptoms persist or worsen.
If pregnant or breastfeeding, ask a health professional before use.
Keep out of reach of children. In case of overdose, get medical help or contact
a Poison Control Center right away.

PREGNANCY OR BREAST FEEDING

If pregnant or breastfeeding, ask a health professional before use.

Keep out of reach of children.

OVERDOSAGE

In case of overdose, get medical help or contact a Poison Control Center right away.

Stop use and ask a doctor if symptoms persist or worsen.

Inactive Ingredients:

Ethanol (beet),
purified water

Other information
Do not use if seal is missing or broken.
Store in a cool, dry place.

Contents may not fill package in order to accommodate required labelling. Please rely on stated quantity.

Directions
Adults and adolescents (12 years and older): Take 5 drops three times daily or as
recommended by your healthcare practitioner.
Children (under 12 years): Take under the direction of your
healthcare practitioner.

Uses
For the temporary relief of symptoms associated with minor stress and mental fatigue.

Directions
Adults and adolescents (12 years and older): Take 5 drops three times daily or as
recommended by your healthcare practitioner.
Children (under 12 years): Take under the direction of your
healthcare practitioner.

Active ingredients
Each drop contains:
Aloe Inspissated juice 6X
Nux vomica (Poison nut) Seed 4X
(2.7 x 10-4 % alkaloids, calculated)
Pulsatilla (Wind Flower) Whole Plant 4X

Uses
For the temporary relief of symptoms associated with mild indigestion.

Warnings
Stop use and ask a doctor if symptoms persist or worsen.
If pregnant or breastfeeding, ask a health professional before use.

Keep out of reach of children. In case of overdose, get medical help or contact
a Poison Control Center right away.

PREGNANCY OR BREAST FEEDING

If pregnant or breastfeeding, ask a health professional before use.

Keep out of reach of children.

OVERDOSAGE

In case of overdose, get medical help or contact a Poison Control Center right away.

Stop use and ask a doctor if symptoms persist or worsen.

Inactive ingredients
Ethanol (beet), purified water

Other information
Do not use if seal is missing or broken.
Store in a cool, dry place.

Directions
Adults and adolescents (12 years and older): Take 5 drops three times daily or as
recommended by your healthcare practitioner.
Children (under 12 years): Take under the direction of your
healthcare practitioner.

Uses

For the temporary relief of symptoms associated with mild indigestion.

Directions
Adults and adolescents (12 years and older): Take 5 drops three times daily or as
recommended by your healthcare practitioner.
Children (under 12 years): Take under the direction of your
healthcare practitioner.

Active ingredients
Each drop contains:
Lactuca virosa
(Poisonous lettuce) Whole Plant 6X
Passiflora incarnata (Passion flower) Aerial Parts 6X
Thymus vulgaris Aerial Parts 6X
Valeriana officinalis (Valerian) Root 6X

PURPOSE

Usea

For the temporary relief of symptoms
associated with mild sleeplessness and nervousness.

Warnings
Stop use and ask a doctor if symptoms
persist or worsen.

If pregnant or breastfeeding, ask a
health professional before use.
Keep out of reach of children. In case
of overdose, get medical help or contact
a Poison Control Center right away.

PREGNANCY OR BREAST FEEDING

If you are pregnant or breastfeeding, ask a healthcare practitioner before use.

Keep out of reach of children.

OVERDOSAGE

In case of overdose, get medical help or contact a Poison Control Center right away.

ASK DOCTOR

If symptoms persist or worsen, consult your healthcare practitioner.

Inactive Ingredients:

Ethanol (beet),
purified water

Other information
Do not use if seal is missing or broken.
Store in a cool, dry place.

Directions
Adults and adolescents (12 years and older): Take 5 drops three times daily or as
recommended by your healthcare practitioner.
Children (under 12 years): Take under the direction of your
healthcare practitioner.

Uses

For the temporary relief of symptoms
associated with mild sleeplessness and nervousness.

Directions
Adults and adolescents (12 years and older): Take 5 drops three times daily or as
recommended by your healthcare practitioner.
Children (under 12 years): Take under the direction of your
healthcare practitioner.

PACKAGE LABEL

NDC 62106-1101-8

UNDA

numbered compounds

UNDA 2

Homeopathic Preparation

For the temporary relief of symptoms
associated with minor fever.

Contains 31% Alcohol

0.7 fl oz (20 ml)

PACKAGE LABEL

NDC 62106-1105-8

UNDA

numbered compounds

UNDA 6

Homeopathic Preparation

For the temporary relief of symptomsassociated

with occasional constipation and flatulence.

Contains 31% Alcohol

0.7 fl oz (20 ml)

PACKAGE LABEL

NDC 62106-1108-8

UNDA

numbered compounds

UNDA 9

Homeopathic Preparation

For the temporary relief of symptoms associated

with minor stress and mental fatigue.

Contains 31% Alcohol
0.7 fl oz (20 ml)

PACKAGE LABEL

NDC 62106-1168-8

UNDA

numbered compounds

UNDA 295

Homeopathic Preparation

For the temporary relief of symptoms
associated with mild indigestion.

Contains 31% Alcohol

0.7 fl oz (20 ml)

PACKAGE LABEL

NDC 62106-1174-8

UNDA

numbered compounds

UNDA 1001

Homeopathic Preparation

For the temporary relief of symptoms
associated with mild sleeplessness and
nervousness.

Contains 31% Alcohol
0.7 fl oz (20 ml)